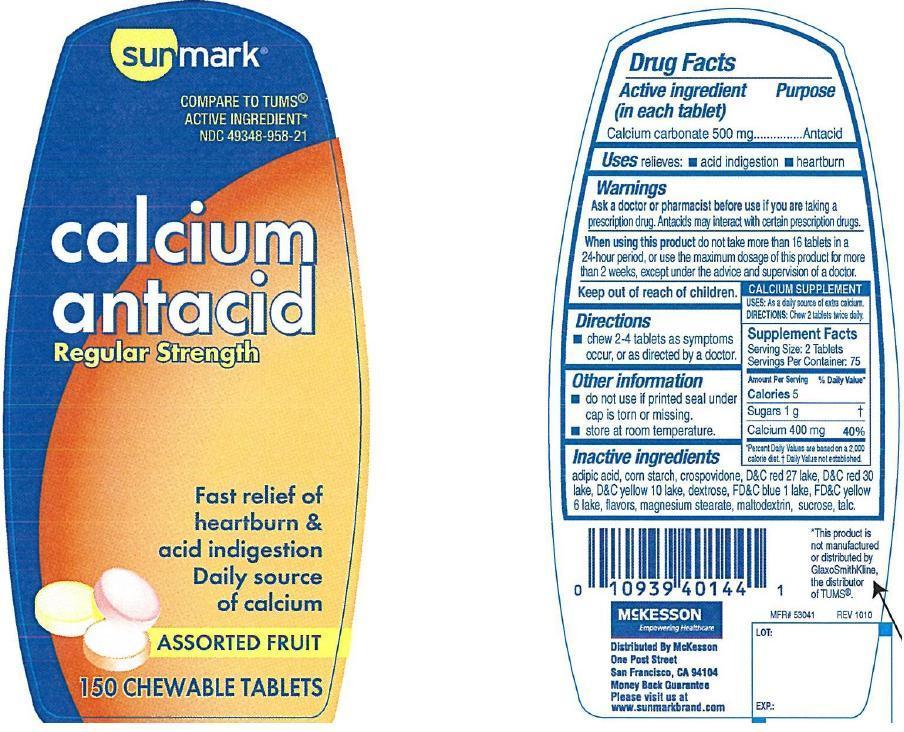 DRUG LABEL: Sunmark calcium antacid
NDC: 49348-958 | Form: TABLET, CHEWABLE
Manufacturer: McKesson
Category: otc | Type: HUMAN OTC DRUG LABEL
Date: 20140408

ACTIVE INGREDIENTS: CALCIUM CARBONATE 500 mg/1 1
INACTIVE INGREDIENTS: ADIPIC ACID; STARCH, CORN; CROSPOVIDONE; D&C RED NO. 27; D&C RED NO. 30; D&C YELLOW NO. 10; DEXTROSE; FD&C BLUE NO. 1; FD&C YELLOW NO. 6; MAGNESIUM STEARATE; MALTODEXTRIN; SUCROSE; TALC

Calcium antacid regular strength

Active ingredient (in each tablet)

Calcium carbonate 500 mg

Purpose

Antacid

Uses

relieves

- acid indigestion
- heartburn

Warnings

Ask a doctor or pharmacist before use if you are

taking a prescription drug. Antacids may interact with certain prescriptiom drugs.

When using this product

do not take more than 16 tablets in a 24-hour period, or use the maximum dosage of this product for more than 2 weeks, except under the advice and supervision of a doctor.

Directions

- chew 2-4 tablets as symptoms occur, or as directed by a doctor

Other information

- do not use if seal under cap is torn or missing
- store at room temperature

Inactive ingredients

adipic acid, corn starch, crospovidone, D and C red 27 lake, D and C red 30 lake, D and C Yellow 10 lake, dextrose, FD and C blue 1 lake, FD and C yellow 6 lake, flavors, magnesium stearate, maltodextrin, sucrose, talc

Principal Display Panel

Sunmark

compare to Tums active ingredient

calcium antacid

regular strength

fast relief of heartburn and acid indigestion

daily source of calcium

assorted fruit flavors

150 chewable tablets